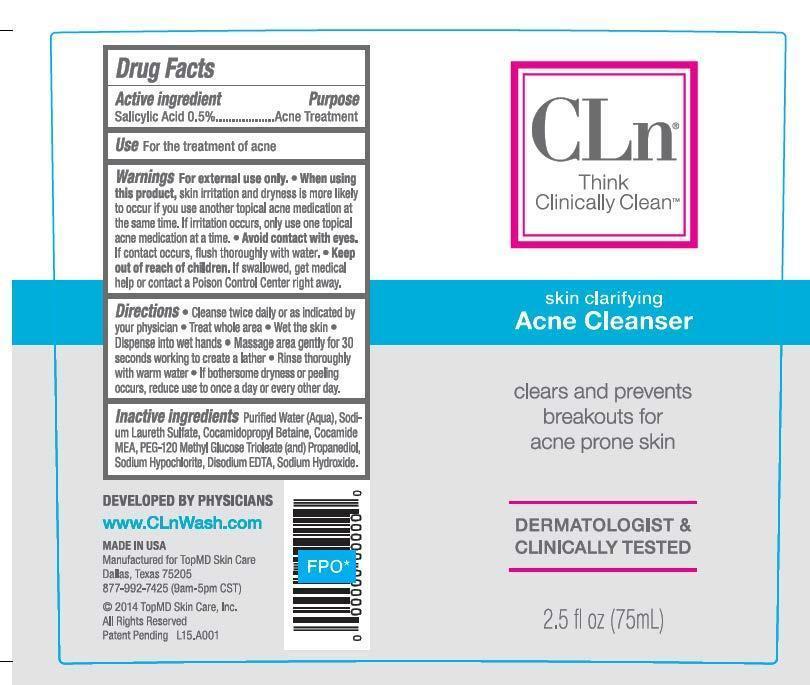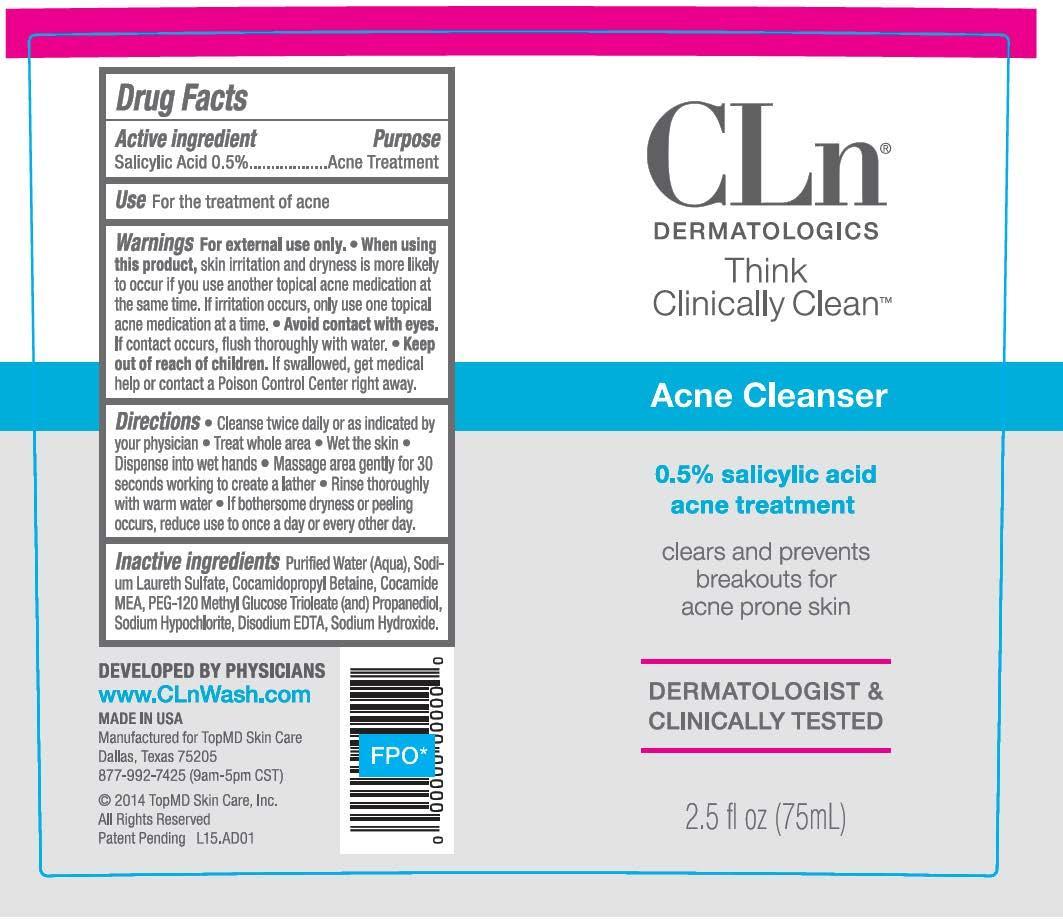 DRUG LABEL: CLn Acne Cleanser
NDC: 69530-856 | Form: LIQUID
Manufacturer: TopMD Skin Care
Category: otc | Type: HUMAN OTC DRUG LABEL
Date: 20150123

ACTIVE INGREDIENTS: SALICYLIC ACID 5 mg/1 mL
INACTIVE INGREDIENTS: COCAMIDOPROPYL BETAINE; COCO MONOETHANOLAMIDE; SODIUM HYPOCHLORITE; EDETATE DISODIUM; SODIUM LAURETH SULFATE; WATER; POLYETHYLENE GLYCOLS; SODIUM HYDROXIDE

CLn Acne Cleanser

Drug Facts

Active ingredient

Salicylic Acid 0.5%

Purpose

Acne Treatment

Use

For the treatment of acne

Warnings

For external use only.

When using this product,

skin irritation and dryness is more likely to occur if you use another topical acne medication at the same time. If irritation occurs, only use on topical acne medication at a time.

- Avoid contact with eyes. If contact occurs, flush thoroughly with water.

Keep out of reach of children.

If swallowed, get medical help or contact a Poison Control Center right away.

Directions

- Cleanse twice daily or as indicated by your physician
- Treat whole area
- Wet the skin
- Dispense into wet hands
- Massage area gently for 30 seconds working to create a lather
- Rinse thoroughly with warm water
- If bothersome dryness or peeling occurs, reduce use to once a day or every other day.

Inactive ingredients

Purified Water (Aqua), Sodium Laureth Sulfate, Cocamidopropyl Betaine, Cocamide MEA, PEG-120 Methyl Glucose Trioleate (and) Propanediol, Sodium Hypochlorite, Disodium EDTA, Sodium Hydroxide

CLn Acne Cleanser

CLn®

Think Clinically Clean™

Skin Clarifying Acne Cleanser

Clears and prevents breakouts for acne prone skin

Dermatologist & clinically tested

2.5 fl oz (75 mL)

CLn Dermatologics

CLn®

Dermatologics

Think Clinically Clean™

Acne Cleanser

0.5% salicylic acid acne treatment

Clears and prevents breakouts for acne prone skin

Dermatologist & Clinically Tested

2.5 fl oz (75 mL)